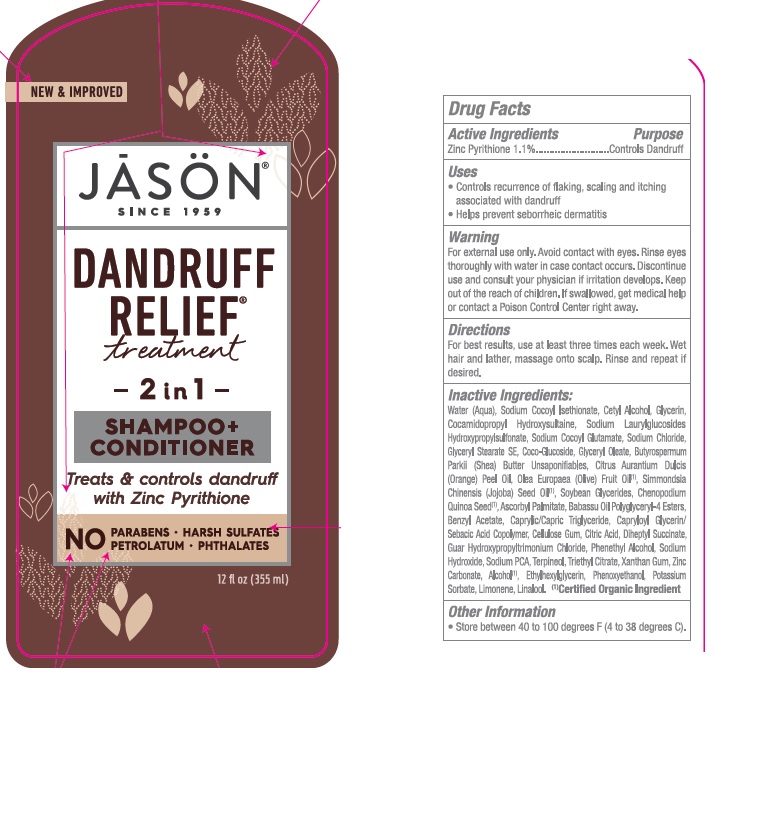 DRUG LABEL: J1002901Jason Dandruff Relief 2in1Treatment
NDC: 61995-0129 | Form: SHAMPOO
Manufacturer: The Hain Celestial Group, Inc.
Category: otc | Type: HUMAN OTC DRUG LABEL
Date: 20210412

ACTIVE INGREDIENTS: PYRITHIONE ZINC 1 g/100 g
INACTIVE INGREDIENTS: GLYCERYL OLEATE; SODIUM COCOYL GLUTAMATE; SODIUM DECYLGLUCOSIDES HYDROXYPROPYLSULFONATE; SODIUM HYDROXIDE; TRIETHYL CITRATE; ETHYLHEXYLGLYCERIN; PHENOXYETHANOL; POTASSIUM SORBATE; CAPRYLIC/CAPRIC ACID; OLIVE OIL; CELLULOSE, MICROCRYSTALLINE; GUAR HYDROXYPROPYLTRIMONIUM CHLORIDE (1.7 SUBSTITUENTS PER SACCHARIDE); TERPINEOL; XANTHAN GUM; STEARYL ALCOHOL; WATER; SODIUM COCOYL ISETHIONATE; GLYCERIN; CETYL ALCOHOL; BABASSU OIL; JOJOBA OIL; ZINC CARBONATE; DIHEPTYL SUCCINATE; ASCORBYL PALMITATE; COCAMIDOPROPYL HYDROXYSULTAINE; SODIUM CHLORIDE; ANHYDROUS CITRIC ACID; MEDIUM-CHAIN TRIGLYCERIDES; ORANGE OIL; GLYCERYL STEARATE SE; CHENOPODIUM QUINOA SEED; ALCOHOL; BENZYL ACETATE; CAPRYLOYL GLYCERIN/SEBACIC ACID COPOLYMER (2000 MPA.S); ORANGE PEEL; COCO GLUCOSIDE; SHEA BUTTER

Jason 2-in-1 Dandruff Shampoo & Conditioner

ACTIVE INGREDIENT

Zinc Pyrithiopne 1.0%

PURPOSE

Controls Dandruff

INDICATIONS AND USAGE

- Controls recurrence of flaking, scaling and itching associated with dandruff
- Helps prevent seborrheic dermatitis

WARNINGS

For external use only . Avoid contact with eyes.Rinse eyes throughly with water in case contact occurs.Discontinue use and consult your physician if irritation develops.

Keep out of reach of children. If swallowed get medical help or contact Poison Center right away.

DOSAGE AND ADMINISTRATION

For best results use at least three times each week. Wet hair and lather, massage into scalp. Rinse and repeat if desired.

INACTIVE INGREDIENT

Water (Aqua), Sodium Cocoyl Isethionate, Cetyl Alcohol, Glycerin, Cocamidopropyl Hydroxysultaine, Sodium Laurylglucosides Hydroxypropylsulfonate, Sodium Cocoyl Glutamate, Sodium Chloride, Glyceryl Stearate SE, Coco-Glucoside, Glyceryl Oleate, Butyrospermum Parkii (Shea) Butter Unsaponifiables, Citrus Aurantium Dulcis (Orange) Peel Oil, Olea Europaea (Olive) Fruit Oil (1), Simmondsia Chinensis (Jojoba) Seed Oil (1), Soybean Glycerides, Chenopodium Quinoa Seed (1), Ascorbyl Palmitate, Babassu Oil Polyglyceryl-4 Esters, Benzyl Acetate, Caprylic/Capric Triglyceride, Capryloyl Glycerin/Sebacic Acid Copolymer, Cellulose Gum, Citric Acid, Diheptyl Succinate, Guar Hydroxypropyltrimonium Chloride, Phenethyl Alcohol, Sodium Hydroxide, Sodium PCA, Terpineol, Triethyl Citrate, Xanthan Gum, Zinc Carbonate, Alcohol (1), Ethylhexylglycerin, Phenoxyethanol, Potassium Sorbate, Limonene, Linalool.

(1) Certified Organic Ingredients